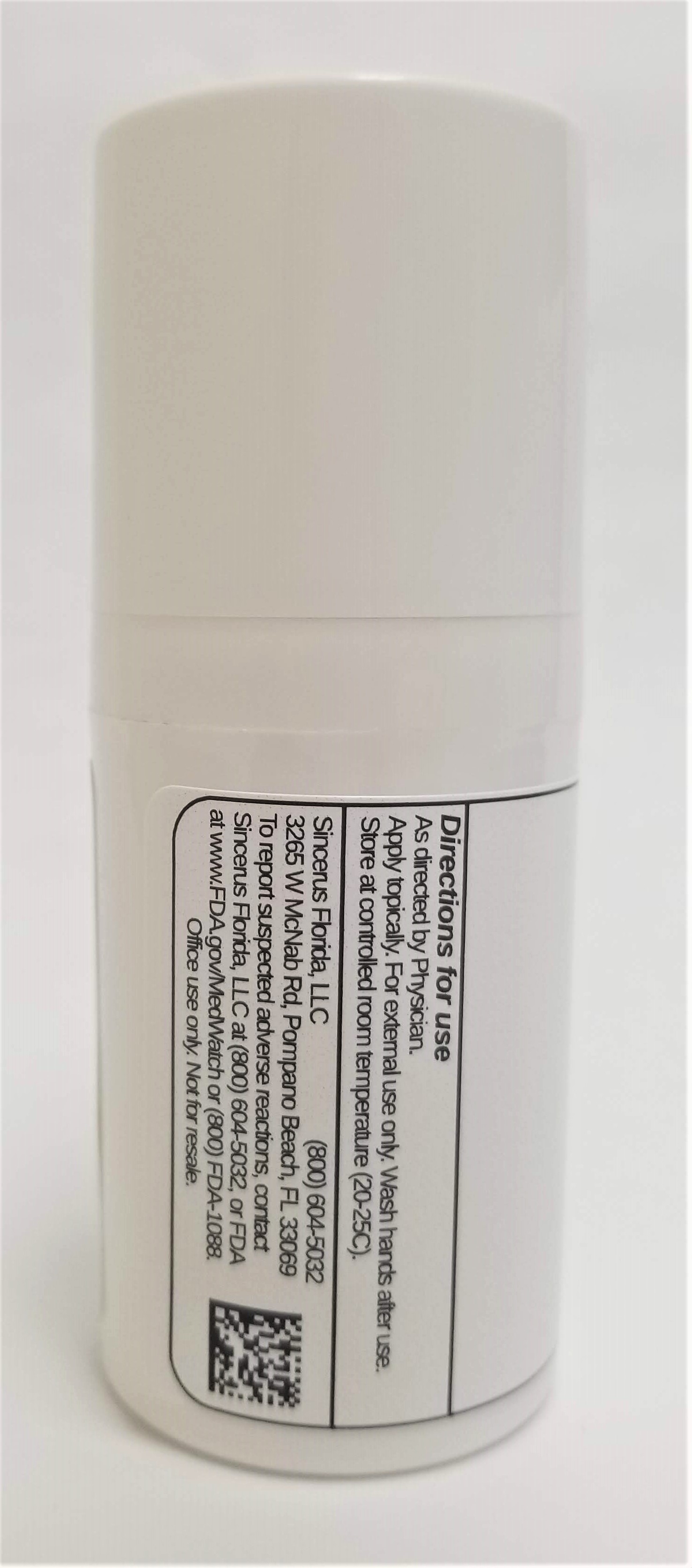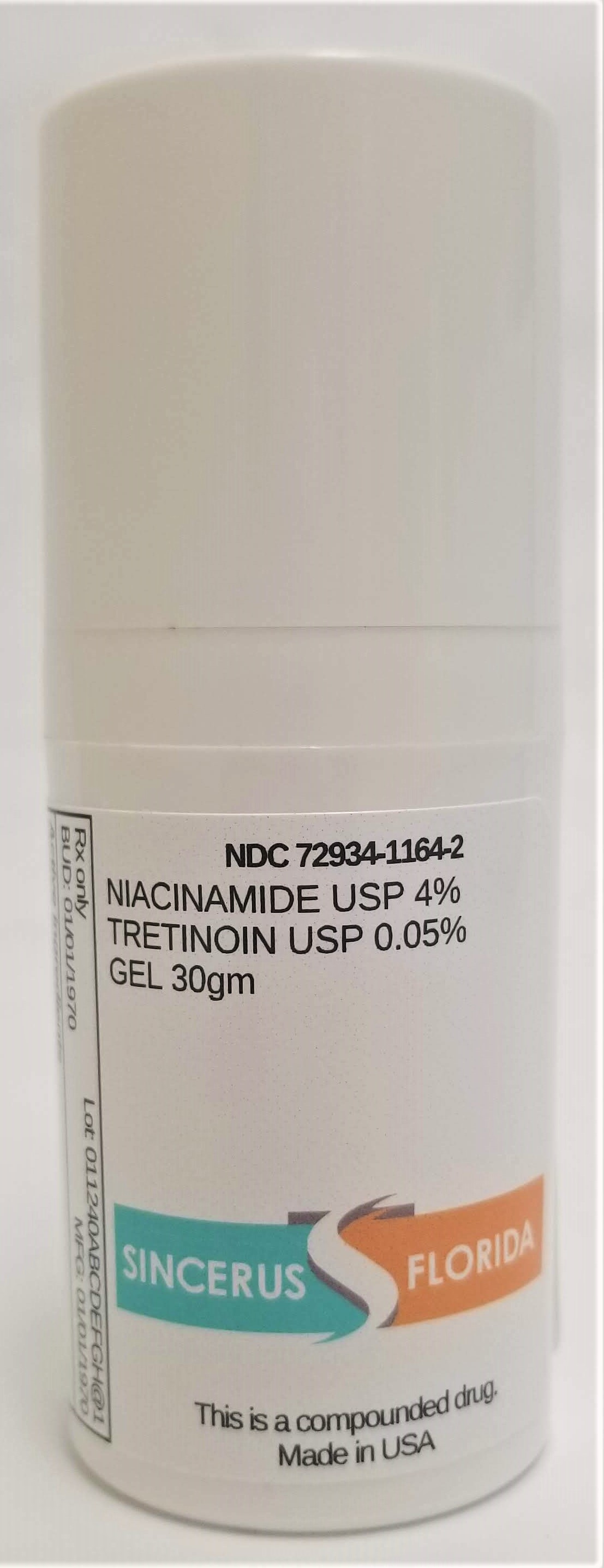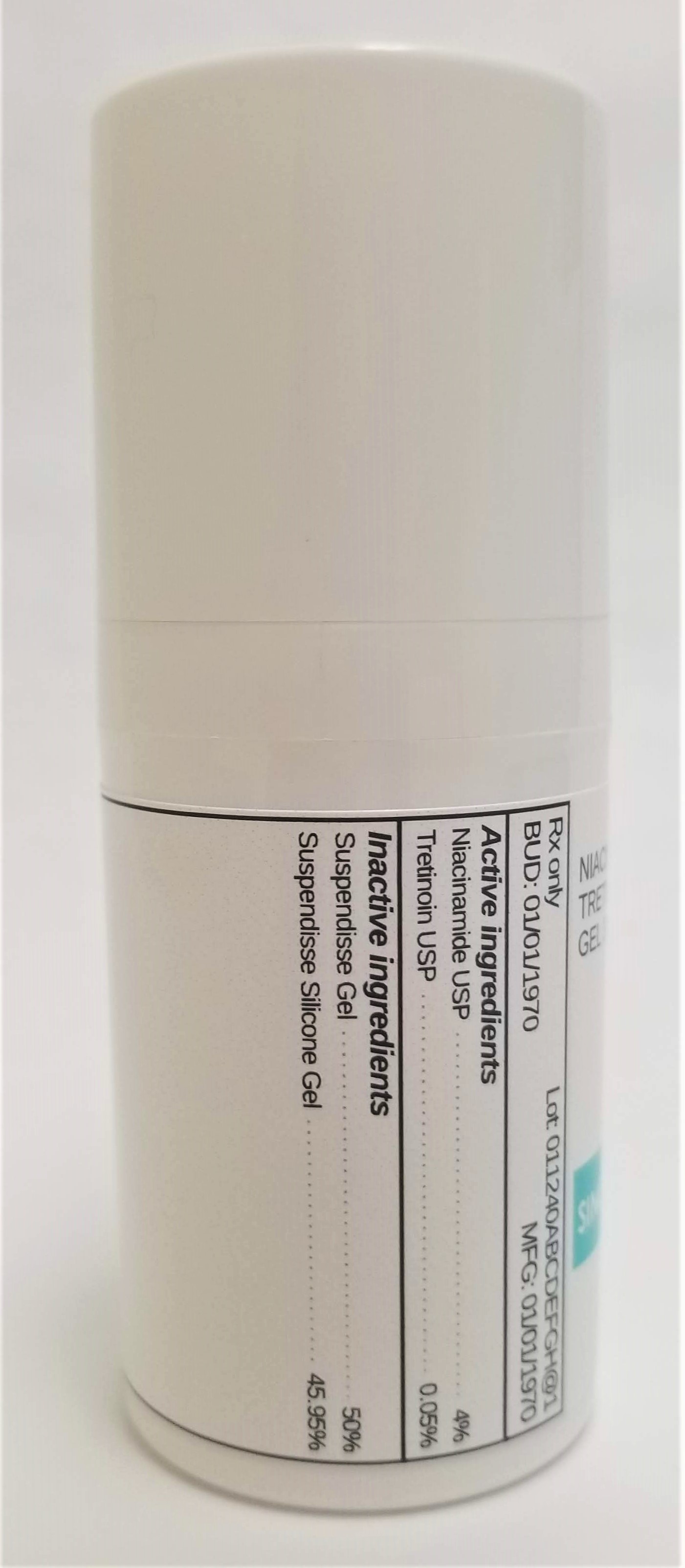 DRUG LABEL: NIACINAMIDE 4% / TRETINOIN 0.05%
NDC: 72934-1164 | Form: GEL
Manufacturer: Sincerus Florida, LLC
Category: prescription | Type: HUMAN PRESCRIPTION DRUG LABEL
Date: 20190503

ACTIVE INGREDIENTS: TRETINOIN 0.05 g/100 g; NIACINAMIDE 4 g/100 g

NIACINAMIDE 4% / TRETINOIN 0.05%